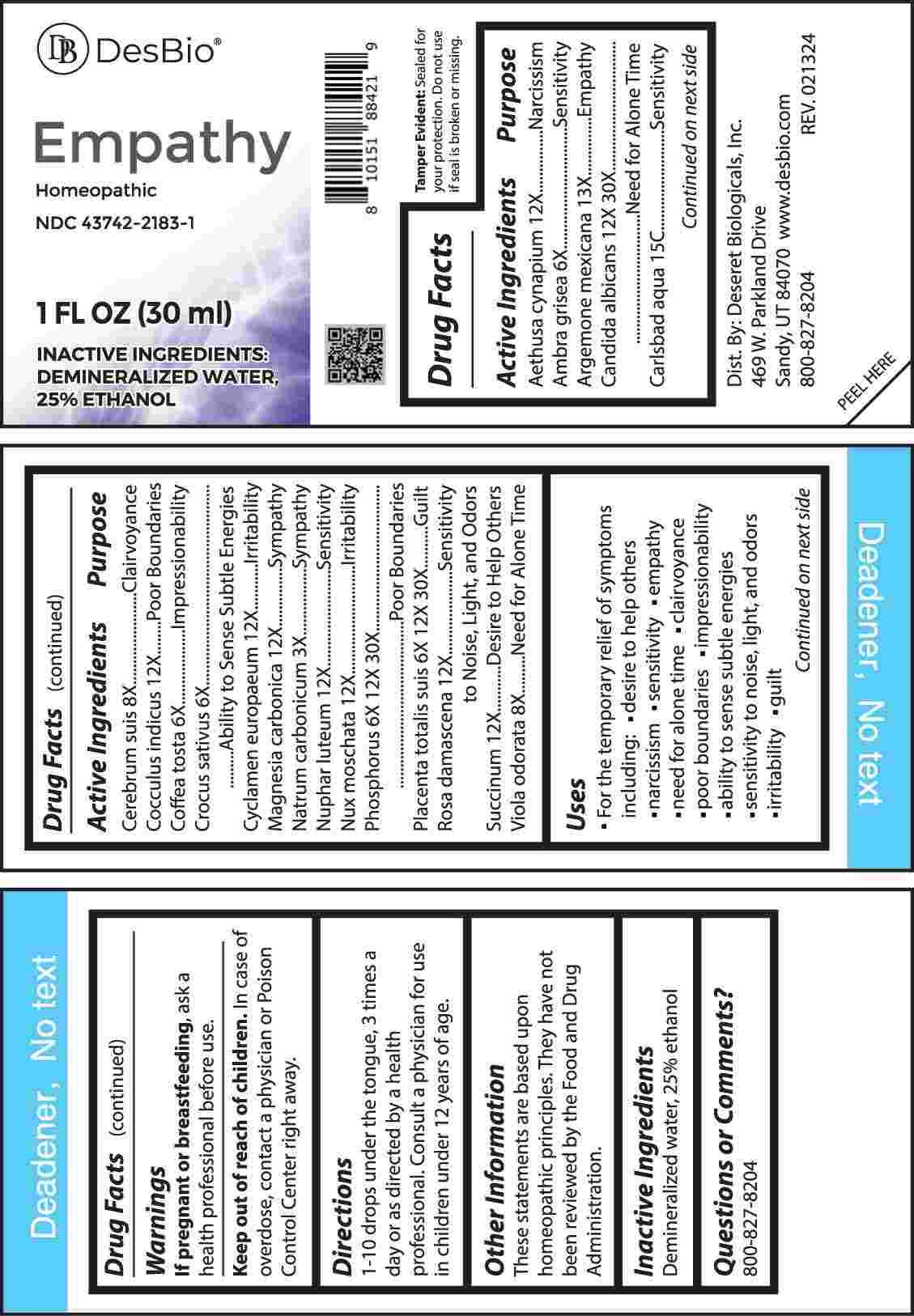 DRUG LABEL: Empathy
NDC: 43742-2183 | Form: LIQUID
Manufacturer: Deseret Biologicals, Inc.
Category: homeopathic | Type: HUMAN OTC DRUG LABEL
Date: 20240813

ACTIVE INGREDIENTS: AETHUSA CYNAPIUM WHOLE 12 [hp_X]/1 mL; AMBERGRIS 6 [hp_X]/1 mL; ARGEMONE MEXICANA 13 [hp_X]/1 mL; CANDIDA ALBICANS 12 [hp_X]/1 mL; WATER 15 [hp_C]/1 mL; SUS SCROFA CEREBRUM 8 [hp_X]/1 mL; ANAMIRTA COCCULUS SEED 12 [hp_X]/1 mL; COFFEA ARABICA SEED, ROASTED 6 [hp_X]/1 mL; SAFFRON 6 [hp_X]/1 mL; CYCLAMEN PURPURASCENS TUBER 12 [hp_X]/1 mL; MAGNESIUM CARBONATE 12 [hp_X]/1 mL; SODIUM CARBONATE 3 [hp_X]/1 mL; NUPHAR LUTEA ROOT 12 [hp_X]/1 mL; NUTMEG 12 [hp_X]/1 mL; PHOSPHORUS 6 [hp_X]/1 mL; SUS SCROFA PLACENTA 6 [hp_X]/1 mL; ROSA X DAMASCENA FLOWERING TOP 12 [hp_X]/1 mL; AMBER 12 [hp_X]/1 mL; VIOLA ODORATA WHOLE 8 [hp_X]/1 mL
INACTIVE INGREDIENTS: ALCOHOL

DRUG FACTS:

ACTIVE INGREDIENTS:

Aethusa Cynapium 12X, Ambra Grisea 6X, Argemone Mexicana 13X, Candida Albicans 12X, 30X, Carlsbad Aqua 15C, Cerebrum Suis 8X, Cocculus Indicus 12X, Coffea Tosta 6X, Crocus Sativus 6X, Cyclamen Europaeum 12X, Magnesia Carbonica 12X, Natrum Carbonicum 3X, Nuphar Luteum 12X, Nux Moschata 12X, Phosphorus 6X, 12X, 30X, Placenta Totalis Suis 6X, 12X, 30X, Rosa Damascena 12X, Succinum 12X, Viola Odorata 8X.

PURPOSE:

Aethusa Cynapium - Narcissism, Ambra Grisea - Sensitivity, Argemone Mexicana - Empathy, Candida Albicans – Need for Alone Time, Carlsbad Aqua - Sensitivity, Cerebrum Suis - Clairvoyance, Cocculus Indicus – Poor Boundaries, Coffea Tosta - Impressionability, Crocus Sativus – Ability to Sense Subtle Energies, Cyclamen Europaeum - Irritability, Magnesia Carbonica – Sympathy, Natrum Carbonicum - Sympathy, Nuphar Luteum - Sensitivity, Nux Moschata - Irritability, Phosphorus – Poor Boundaries, Placenta Totalis Suis – Guilt , Rosa Damascena – Sensitivity to Noise, Light, and Odors, Succinum – Desire to Help Others, Viola Odorata – Need for Alone Time

USES:

• For the temporary relief of symptoms including:

• desire to help others • narcissism • sensitivity • empathy

• need for alone time • clairvoyance • poor boundaries

• impressionability • ability to sense subtle energies

• sensitivity to noise, light, and odors • irritability • guilt

These statements are based upon homeopathic principles. They have not been reviewed by the Food and Drug Administration.

WARNINGS:

If pregnant or breast-feeding, ask a health professional before use.

Keep out of reach of children. In case of overdose, contact a physician or Poison Control Center right away.

Tamper Evident: Sealed for your protection. Do not use if seal is broken or missing.

KEEP OUT OF REACH OF CHILDREN:

In case of overdose, contact a physician or Poison Control Center right away.

DIRECTIONS:

1-10 drops under the tongue, 3 times a day or as directed by a health professional. Consult a physician for use in children under 12 years of age.

INACTIVE INGREDIENTS:

Demineralized water, 25% ethanol

QUESTIONS:

Dist. By: Deseret Biologicals, Inc.

469 W. Parkland Drive

Sandy, UT 84070

www.desbio.com

800-827-8204

PACKAGE LABEL DISPLAY:

DesBio

Empathy

Homeopathic

NDC 43742-2183-1

1 FL OZ (30 ml)